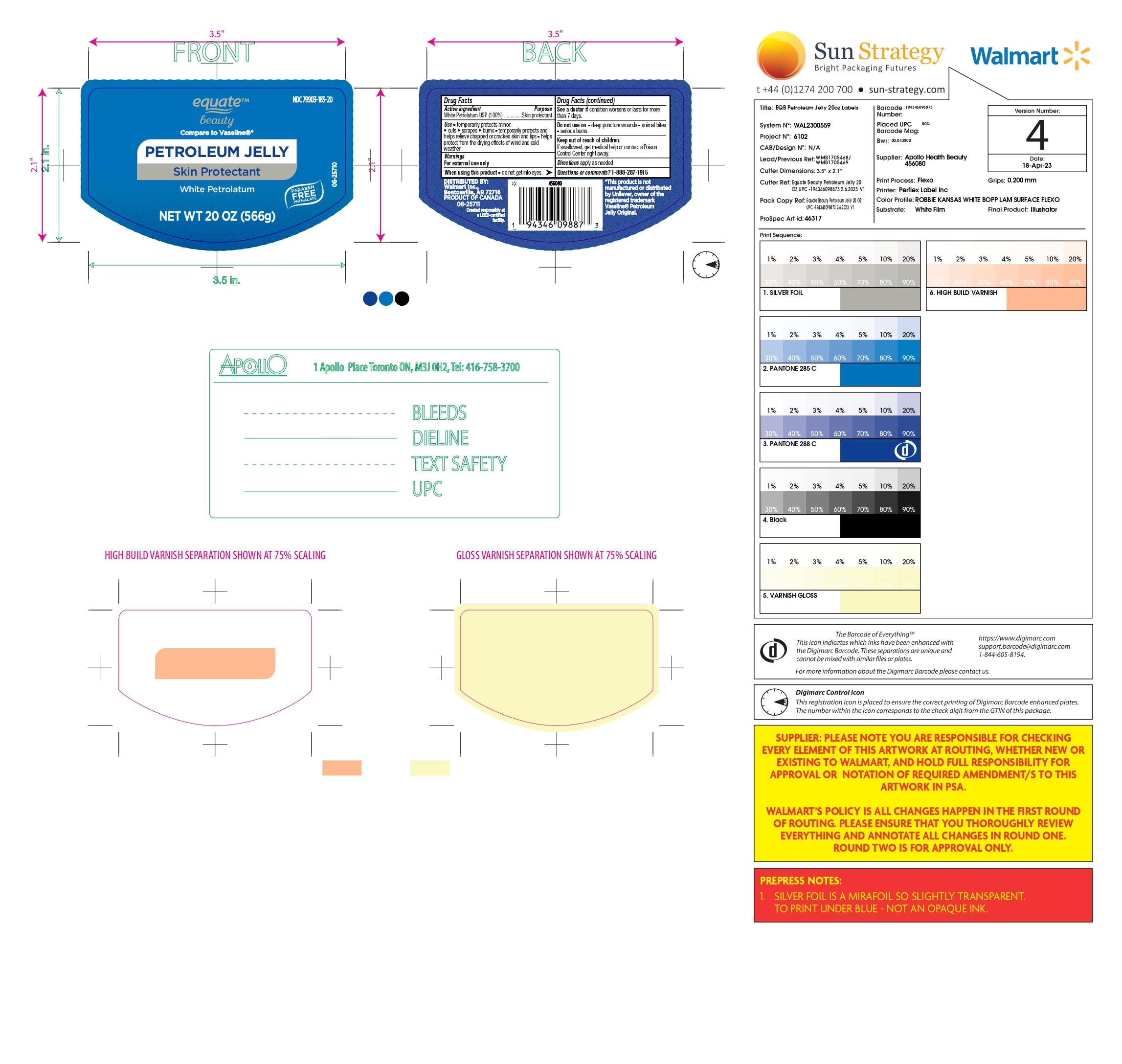 DRUG LABEL: Petroleum Jelly
NDC: 79903-183 | Form: JELLY
Manufacturer: Walmart INC
Category: otc | Type: HUMAN OTC DRUG LABEL
Date: 20250103

ACTIVE INGREDIENTS: WHITE PETROLATUM 100 g/100 g

White Petrolatum

Active Ingredient

White Petrolatum USP (100%)

Purpose

Skin protectant

Uses

temporarily protects minor:

- cuts
- scrapes
- burns
- temporarily protects and helps relieve chapped or cracked skin and lips.
- helps protect from the drying effects of wind and cold weather.

Warnings

For External use only

When using this product

- do not get into eyes

See a doctor if conditions worsen or lasts for more than 7 days

Do not use on

- Deep puncture wounds
- animal bites
- serious burns

Keep out of Reach of Children

If swallowed, get medical help or contact a Poison Control Center right away.

Directions

Directions- Apply as needed

Inactive Ingredients

No Inactive Ingredients

Questions or comments?

1-888-287-1915